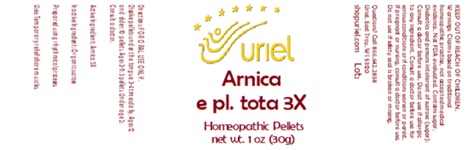 DRUG LABEL: Arnica e pl. tota 3
NDC: 48951-1128 | Form: PELLET
Manufacturer: Uriel Pharmacy Inc.
Category: homeopathic | Type: HUMAN OTC DRUG LABEL
Date: 20250627

ACTIVE INGREDIENTS: ARNICA MONTANA 3 [hp_X]/1 1
INACTIVE INGREDIENTS: SUCROSE

Arnica e pl. tota 3

INDICATIONS AND USAGE

Directions: FOR ORAL USE ONLY.

DOSAGE AND ADMINISTRATION

Dissolve pellets under the tongue 3-4 times daily. Ages 12 and older: 10 pellets. Ages 2-11: 5 pellets. Under age 2: Consult a doctor.

Active Ingredient: Arnica 3X

Inactive Ingredient: Organic sucrose

Prepared using rhythical processes.

PURPOSE

Uses: Temporary relief of sore muscles.

KEEP OUT OF REACH OF CHILDREN.

WARNINGS

Warnings: Claims based on traditional homeopathic practice, not accepted medical evidence. Not FDA evaluated. Contains sugar. Diabetics and persons intolerant of sucrose (sugar): Consult a doctor before use. Do not use if allergic to any ingredient. Consult a doctor before use for serious conditions or if conditions worsen or persist. If pregnant or nursing, consult a doctor before use. Do not use if safety seal is broken or missing.

Questions? Call 866.642.2858
Uriel, East Troy, WI 53120
shopuriel.com Lot: